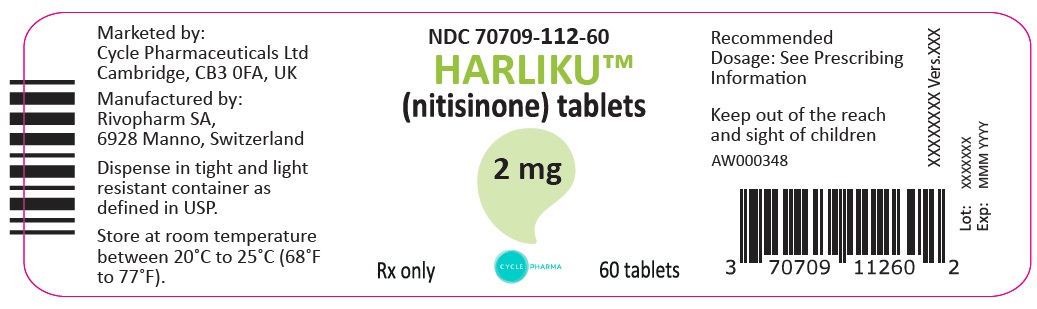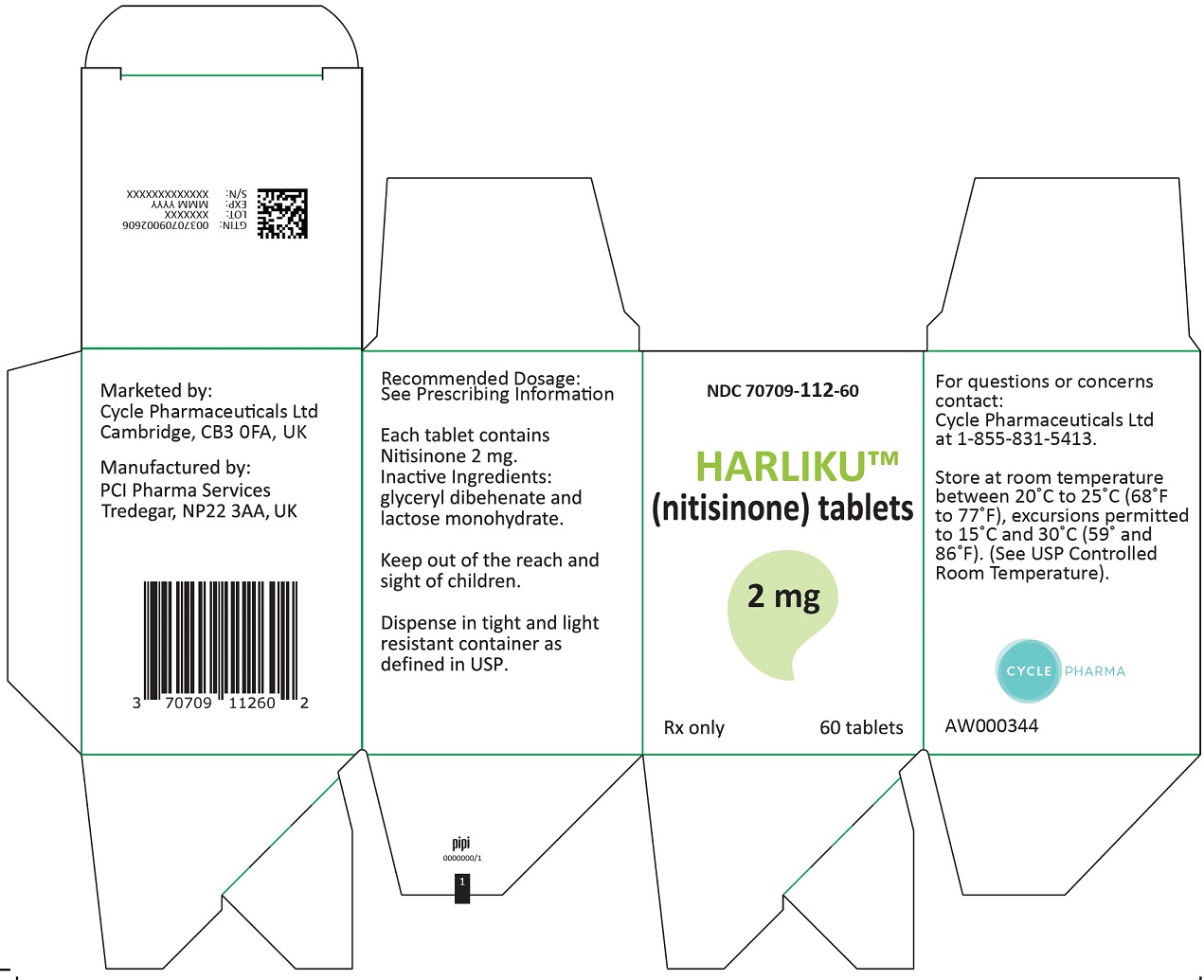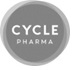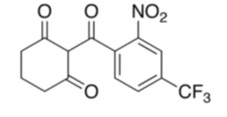 DRUG LABEL: HARLIKU
NDC: 70709-112 | Form: TABLET
Manufacturer: Cycle Pharmaceuticals Ltd.
Category: prescription | Type: HUMAN PRESCRIPTION DRUG LABEL
Date: 20250602

ACTIVE INGREDIENTS: nitisinone 2 mg/1 1
INACTIVE INGREDIENTS: GLYCERYL DIBEHENATE; LACTOSE MONOHYDRATE

HIGHLIGHTS OF PRESCRIBING INFORMATION

These highlights do not include all the information needed to use HARLIKU safely and effectively. See full prescribing information for HARLIKU.
HARLIKUTM (nitisinone) tablets, for oral use
Initial U.S. Approval: 2002

1 INDICATIONS AND USAGE

HARLIKU is a hydroxyphenyl-pyruvate dioxygenase inhibitor indicated for the reduction of urine homogentisic acid (HGA) in adult patients with alkaptonuria (AKU). (1)

2 DOSAGE AND ADMINISTRATION

The recommended dosage of HARLIKU is 2 mg administered orally, once daily. (2.1)

3 DOSAGE FORMS AND STRENGTHS

Tablets: 2 mg. (3)

4 CONTRAINDICATIONS

None. (4)

5 WARNINGS AND PRECAUTIONS

Ocular Symptoms and Hyperkeratotic Plaques Due To Elevated Plasma Tyrosine Levels: Inadequate restriction of tyrosine and phenylalanine intake can lead to elevations in plasma tyrosine and levels above 500 micromol/L may lead to ocular signs and symptoms or painful hyperkeratotic plaques on the soles and palms. (5.1)

- Assess plasma tyrosine levels in patients presenting with ocular signs and symptoms. (5.1)
- Obtain slit-lamp examination prior to treatment and regularly thereafter. (5.1)
- Implement diet restriction and/or treatment interruption as appropriate. (5.1)

Leukopenia and Severe Thrombocytopenia: Monitor platelet and white blood cell counts. (5.2)

6 ADVERSE REACTIONS

Most common adverse reactions (>1%) are elevated tyrosine levels, keratitis and thrombocytopenia. (6.1)

To report SUSPECTED ADVERSE REACTIONS, contact Cycle Pharmaceuticals Ltd at 1-855-831-5413 or FDA at 1-800-FDA-1088 or www.fda.gov/medwatch.

7 DRUG INTERACTIONS

Sensitive CYP2C9 Substrates: Reduce dosage of co-administered drug metabolized by CYP2C9 by half. (7.1)

OAT1/OAT3 Substrates: Avoid concomitant use of HARLIKU with OAT1/OAT3 substrates. Concomitant use with OAT1/OAT3 substrates may increase the risk of adverse reactions related to the co-administered drug. (7.1)

FULL PRESCRIBING INFORMATION

1 INDICATIONS AND USAGE

HARLIKUTM is indicated for the reduction of urine homogentisic acid (HGA) in adult patients with alkaptonuria (AKU).

2 DOSAGE AND ADMINISTRATION

2.1 Recommended Dosage

The recommended dosage of HARLIKU is 2 mg administered orally, once daily.

Administer HARLIKU with or without food [see Clinical Pharmacology (12.3)].

Missed Dose
If a dose of HARLIKU is missed, do not administer two doses at once to make up for a missed dose. Take the next dose at the scheduled time.

3 DOSAGE FORMS AND STRENGTHS

Tablets: 2 mg white to beige, round, flat tablets, which may display light yellow to brown speckles, debossed with “2” mg on one side and “L” on the other side.

4 CONTRAINDICATIONS

None.

5 WARNINGS AND PRECAUTIONS

5.1 Ocular Symptoms and Hyperkeratotic Plaques Due to Elevated Plasma Tyrosine Levels

Treatment with HARLIKU may cause elevated plasma tyrosine levels in patients with AKU. Tyrosine levels greater than 500 micromol/L may lead to the following:

- Ocular signs and symptoms including keratitis, corneal opacities, corneal irritation, corneal ulcers, conjunctivitis, eye pain, and photophobia. These ocular adverse reactions have been reported in patients treated with nitisinone [see Adverse Reactions (6.1)]. In a clinical trial in the AKU population, without dietary restriction and reported tyrosine levels > 500 micromol/L, both symptomatic and asymptomatic keratopathies have been observed. Perform a baseline ophthalmologic examination including slit-lamp examination prior to initiating HARLIKU treatment and regularly thereafter. Patients who develop photophobia, eye pain, or signs of inflammation such as redness, swelling, or burning of the eyes or tyrosine levels are > 500 micromol/L during treatment with HARLIKU should undergo slit-lamp re-examination and immediate measurement of the plasma tyrosine concentration.

- Painful hyperkeratotic plaques on the soles and palms.

There is no routine dietary restriction requirement for AKU patients taking HARLIKU. However, in patients who develop keratopathies, monitor plasma tyrosine levels, and implement a diet restricted in tyrosine and phenylalanine to keep the plasma tyrosine level below 500 micromol/L. Consider temporarily interrupting HARLIKU until resolution of symptoms.

5.2 Leukopenia and Severe Thrombocytopenia

In clinical trials, patients with hereditary tyrosinemia type 1 (HT-1) treated with another oral formulation of nitisinone and dietary restriction developed reversible leukopenia (3%), thrombocytopenia (3%), or both (1.5%). Ten percent of patients in Trial 1 developed thrombocytopenia [see Adverse Reactions (6.1)]. No patients developed infections or bleeding as a result of the episodes of leukopenia and thrombocytopenia. Monitor platelet and white blood cell counts during HARLIKU therapy.

6 ADVERSE REACTIONS

Serious and/or clinically significant adverse reactions described elsewhere in labeling include:

- Ocular Symptoms and Hyperkeratotic Plaques Due to Elevated Plasma Tyrosine Levels [see Warnings and Precautions (5.1)]
- Leukopenia and Severe Thrombocytopenia [see Warnings and Precautions (5.2)]

6.1 Clinical Trials Experience

Because clinical trials are conducted under widely varying conditions, adverse reaction rates observed in the clinical trials of a drug cannot be directly compared to rates in the clinical trials of another drug and may not reflect the rates observed in practice.

The safety of HARLIKU was evaluated in Trial 1, a three-year, open-label, randomized, no-treatment controlled trial in 40 patients with AKU. Patients were between 38 and 68 years of age (27 male, 13 female) [see Clinical Studies (14)]. Patients received either HARLIKU 2 mg orally once daily or no treatment [see Dosage and Administration (2)].

The serious adverse reactions reported with HARLIKU were ocular/visual complaints associated with elevated tyrosine levels (keratitis) [see Warnings and Precautions (5.1)]. Keratitis led to permanent treatment discontinuation in 1 (5%) treated patient.

The most common adverse reactions (>1%) reported in Trial 1 are summarized in TABLE 1.

TABLE 1. Most Common Adverse Reactions* in Patients with AKU Treated with Nitisinone**

Adverse Reactions | Nitisinone; (N=20); n (%) | No Treatment; (N=20); n (%)
Elevated tyrosine levels | 19 (95) | 0 (0)
Keratitis*** | 3 (15) | 0 (0)
Thrombocytopenia | 2 (10) | 0 (0)

* reported in at least 1% of patients; ** another oral formulation of nitisinone;
*** keratitis also includes eye irritation, eye pain and photophobia.

7 DRUG INTERACTIONS

7.1 Effects of HARLIKU on Other Drugs

Sensitive CYP2C9 Substrates

Reduce the dosage of the co-administered drug metabolized by CYP2C9 by half. Additional dosage adjustments may be needed to maintain therapeutic drug concentrations where minimal concentration changes may lead to serious adverse reactions. See prescribing information for those drugs.

Nitisinone is a moderate CYP2C9 inhibitor. Nitisinone may increase exposure of co-administered drugs metabolized by CYP2C9 [see Clinical Pharmacology (12.3)].

OAT1/OAT3 Substrates

The concomitant use of HARLIKU with OAT1/OAT3 substrates may increase the risk of adverse reactions related to the co-administered drug. See prescribing information for those drugs.

Nitisinone is an OAT1/OAT3 inhibitor which can lead to increased exposure of the co-administered drug. [see Clinical Pharmacology (12.3)].

8 USE IN SPECIFIC POPULATIONS

8.1 Pregnancy

Risk Summary
Available data from published case reports with nitisinone use in pregnant women are insufficient to identify a drug-associated risk of major birth defects, miscarriage or other adverse maternal or fetal outcomes. Animal reproduction studies have been conducted for nitisinone. In these studies, nitisinone was administered to mice and rabbits during organogenesis with oral doses of nitisinone up to 600 and 240 times respectively, the maximum recommended human daily dose (MRHDD) of 2 mg/day. In mice, nitisinone caused incomplete skeletal ossification of fetal bones and decreased pup survival at doses 12 times the MRHDD, and increased gestational length at doses 120 times the MRHDD. In rabbits, nitisinone caused maternal toxicity and incomplete skeletal ossification of fetal bones at doses 48 times the MRHDD (see Data).

The background risk of major birth defects and miscarriage for the indicated population is unknown. All pregnancies have a background risk of birth defect, loss, or other adverse outcomes. In the U.S. general population, the estimated background risk of major birth defects and miscarriage in clinically recognized pregnancies is 2 to 4% and 15 to 20%, respectively.

Data

Animal Data

In an embryo-fetal development study in mice, nitisinone was administered via oral gavage to pregnant mice at dose levels of 12, 120 and 600 times the maximum recommended human daily dose (MRHDD) of 2 mg/day. Nitisinone caused incomplete skeletal ossification of fetal bones and decreased pup survival at doses 12 times the MRHDD and increased gestational length at doses 120 times the MRHDD.

In an embryo-fetal development study in rabbits, nitisinone was administered via oral gavage to pregnant rabbits at dose levels of 48, 120 and 240 times the MRHDD of 2 mg/day. Nitisinone caused maternal toxicity and incomplete skeletal ossification of fetal bones at doses 48 times the MRHDD.

In a single dose-group study in rats given 100 mg/kg (486 times the MRHDD of 2 mg/day), reduced litter size, decreased pup weight at birth, and decreased survival of pups after birth was demonstrated.

8.2 Lactation

Risk Summary
There are no data on the presence of nitisinone in human milk, the effects on the breastfed infant, or the effects on milk production. Data suggest that nitisinone is present in rat milk due to findings of ocular toxicity and lower body weight seen in drug naive nursing rat pups. The developmental and health benefits of breastfeeding should be considered along with the mother’s clinical need for HARLIKU and any potential adverse effects on the breastfed infant from HARLIKU or from the underlying maternal condition.

8.4 Pediatric Use

The safety and effectiveness of HARLIKU have not been established in pediatric patients with AKU.

8.5 Geriatric Use

There was 1 patient 65 years of age and older in the clinical studies for AKU [see Clinical Studies (14)]. Of the total number of HARLIKU-treated patients in these studies, 1 (2.5 %) were 65 years of age and older, while 0 (0%) were 75 years of age and older.

Clinical studies of HARLIKU did not include sufficient numbers of patients 65 years of age and older to determine whether they respond differently from younger adult patients.

11 DESCRIPTION

HARLIKU (nitisinone) is a hydroxyphenyl-pyruvate dioxygenase inhibitor.

Nitisinone occurs as a white to yellowish-white, crystalline powder. It is practically insoluble in water, soluble in 2M sodium hydroxide and in methanol, and sparingly soluble in alcohol.

The chemical name of nitisinone is 2-(2-nitro-4-trifluoromethylbenzoyl) cyclohexane-1,3-dione. The molecular formula is C14H10F3NO5 and the molecular weight is 329.23. The structural formula is:

Each HARLIKU (nitisinone) tablet contains 2 mg of nitisinone to be administered orally. The inactive ingredients are glyceryl dibehenate and lactose monohydrate.

12 CLINICAL PHARMACOLOGY

12.1 Mechanism of Action

Nitisinone is a competitive inhibitor of hydroxyphenyl-pyruvate dioxygenase, an enzyme upstream of homogentisate 1,2-dioxygenase (HGD) in the tyrosine catabolic pathway.

12.2 Pharmacodynamics

In patients with AKU, HGA accumulates in various tissues and urine. In an open-label, single center, randomized, no-treatment controlled trial nitisinone treatment resulted in reduction of urinary HGA concentrations in patients with AKU [see Clinical Studies (14)].

Nitisinone exposure-response relationship and time course of pharmacodynamic response for the effectiveness have not been fully characterized.

Nitisinone inhibits catabolism of the amino acid tyrosine and can result in elevated plasma levels of tyrosine in patients with AKU. Treatment with nitisinone does not require routine dietary restriction in patients with AKU; however, patients who develop keratopathies should be monitored and dietary restriction of tyrosine and phenylalanine should be implemented [see Warnings and Precautions (5.1)].

12.3 Pharmacokinetics

The single-dose pharmacokinetics of nitisinone tablets have been studied in healthy adult subjects. Nitisinone pharmacokinetic parameters are presented as geometric mean [range] unless otherwise specified. Nitisinone maximum concentration (Cmax) and area under the curve from time 0 to 120 hours (AUC0-120h) were 1278 [780 to 1649] ng/mL and 77874 [42335 to 104211] ng•h/mL following oral administration of 10 mg (5 times the recommended dosage) nitisinone under fasting conditions.

Absorption

Nitisinone time to Cmax (Tmax) is 3.5 hours (median, ranging from 1 to 4 hours) following single oral administration of 10 mg (5 times the recommended dosage) nitisinone under fasting conditions.

Effect of Food: In a food effect study, a high-fat and high-calorie breakfast (973.6 cal distributed in carbohydrate 250.1 cal, proteins 157 cal, fat 566.5 cal) did not significantly affect the total exposure (AUC0-120h) and Cmax of nitisinone following single oral administration of 10 mg nitisinone (5 times the recommended dosage). The median Tmax was delayed to 6 hours under fed conditions [see Dosage and Administration (2)].

Distribution

The arithmetic mean (SD) apparent volume of distribution of nitisinone is 8.2 (1.6) L in healthy subjects (n=23).

In vitro binding of nitisinone to human plasma proteins is greater than 95% at 50 micromolar concentration.

Elimination

The arithmetic mean (SD) terminal half-life of nitisinone is 59.3 (8.9) hours in healthy subjects (n=23). The mean (CV%) apparent plasma clearance in 18 healthy adults following multiple once daily doses of nitisinone 80 mg (40 times the recommended dosage) is 113 (16) mL/hr. The mean of the fraction of dose excreted renally as unchanged nitisinone in the urine (fe(%)) was 3% (n=3) following multiple oral doses of 80 mg (40 times the recommended dosage) daily in healthy subjects.

Metabolism

In vitro studies have shown that nitisinone is relatively stable in human liver microsomes with minor metabolism possibly mediated by CYP3A4 enzyme.

Excretion

The estimated mean (CV%) renal clearance of nitisinone was 0.003 L/h (25%).

Drug Interaction Studies

Clinical Studies

Nitisinone does not inhibit CYP2D6. Nitisinone is a moderate inhibitor of CYP2C9, and a weak inducer of CYP2E1 (TABLE 2). Nitisinone is an inhibitor of OAT1/3 (TABLE 2).

TABLE 2. Percent Change in AUC0-inf and Cmax for Co-administered Drugs in the Presence of Nitisinone in 18 Healthy Subjects

Co-administered Drug a | Dose of Co-administered Drug (Route of Administration) | Effect of Nitisinone on the Pharmacokinetics of Co-administered Drug b
Co-administered Drug a | Dose of Co-administered Drug (Route of Administration) | AUC0-inf | Cmax
CYP2C9 Substrate Tolbutamide c | 500 mg (oral) | 131%↑ | 16%↑
CYP2E1 Substrate; Chlorzoxazone | 250 mg (oral) | 27%↓ | 18%↓
OAT1/3 Substrate Furosemide | 20 mg (intravenous) | 72%↑ | 12%↑

↑= Increased; ↓= Decreased

a The interacting drug was administered alone on Day 1 and together with nitisinone on Day 17.
b Multiple doses of 80 mg nitisinone (40 times the recommended dosage) were administered daily alone from Day 3 to Day 16.
c 16 subjects in Period 2 received nitisinone and tolbutamide while 18 subjects in Period 1 received nitisinone alone.

In Vitro Studies

CYP450 Enzymes: Nitisinone does not inhibit CYP1A2, 2C19, or 3A4. Nitisinone does not induce CYP1A2, 2B6 or 3A4/5.

Transporter Systems: Nitisinone does not inhibit P-gp, BCRP, OATP1B1, OATP1B3 and OCT2.

13 NONCLINICAL TOXICOLOGY

13.1 Carcinogenesis, Mutagenesis, Impairment of Fertility

The carcinogenic potential of nitisinone was assessed in a 26-week oral (gavage) carcinogenicity study in Tg.rasH2 mice. There were no drug-related neoplastic findings in male or female Tg.rasH2 mice at doses up to 100 mg/kg/day nitisinone (approximately 243 times the maximum recommended human daily dose of 2 mg/day).

Nitisinone was not genotoxic in the Ames test and the in vivo mouse liver unscheduled DNA synthesis (UDS) test. Nitisinone was mutagenic in the mouse lymphoma cell (L5178Y/TK+/-) forward mutation test and in an in vivo mouse bone marrow micronucleus test.

14 CLINICAL STUDIES

The effectiveness of HARLIKU was evaluated in an open-label, single center, randomized, no-treatment controlled trial in 40 adult patients diagnosed with AKU (NCT00107783). Patients received either HARLIKU at 2 mg orally once daily or no treatment for three years.

One patient in the HARLIKU group died after experiencing atrial fibrillation and had discontinued treatment one month prior to death, and 2 patients in the no treatment control group discontinued the study early. Among the 40 patients enrolled in the trial, 27 (67.5%) were male and 13 (32.5%) were female, ranging in age from 38 to 68 with a mean age of 51.7 years. Thirty-seven (92.5%) patients were White, 2 (5%) were Asian, and 1 (2.5%) was American Indian or Alaska Native. Thirty-nine (97.5%) patients were not Hispanic or Latino and 1 (2.5%) patient was Hispanic or Latino.

HARLIKU was effective at reducing levels of urinary HGA. The HARLIKU group had an average percent reduction from baseline of 88% (95% CI: 79, 97%) after 1 year of treatment, which was sustained through three years of treatment with an average percent reduction from baseline of 91% at year 3 (95% CI: 85, 97%). In contrast, the untreated controls had an average increase of 107% from baseline to year 1 (95% CI: 0, 216%) and 108% from baseline to year 3 (95% CI: 19, 198%).

16 HOW SUPPLIED/STORAGE AND HANDLING

How Supplied

HARLIKU (nitisinone) tablet is white to beige, round, flat which may display light yellow to brown speckles, debossed with the “strength” in mg on one side and “L” on the other side. Each tablet contains 2 mg nitisinone.

HARLIKU is supplied in a high-density polyethylene (HDPE) square bottle with a child-resistant tamper-evident polypropylene (PP) screw cap. Each bottle contains 60 tablets.

2 mg tablets: NDC 70709-112-60

Storage and Handling

Store HARLIKU tablets at room temperature between 20°C to 25°C (68°F to 77°F); excursions permitted between 15°C and 30°C (59°F and 86°F) [see USP Controlled Room Temperature].

Pharmacist: Dispense in tight and light resistant container as defined in USP.

17 PATIENT COUNSELING INFORMATION

Ocular Symptoms and Hyperkeratotic Plaques Due to Elevated Plasma Tyrosine Levels

Advise the patient or caregiver to report any unexplained ocular or other symptoms promptly to their healthcare provider [see Warnings and Precautions (5.1)].

How Supplied/Storage and Handling

Advise the patient or caregiver to store HARLIKU in the container that it is dispensed in and keep the container tightly closed [see How Supplied/Storage and Handling (16)].

Manufactured by:
PCI Pharma Services
23-24 Tafarnaubach Industrial Estate
Tredegar, Gwent
NP22 3AA, United Kingdom

Rivopharm SA
Centro Insema
6928 Manno, Switzerland

Marketed by:
Cycle Pharmaceuticals Ltd
The Broers Building
21 JJ Thomson Ave
Cambridge, CB3 0FA, United Kingdom

Patented: see www.cyclepharma.com/product-patent-information

Principal Display Panel - 2 mg Carton Label

NDC 70709-112-60

HARLIKUTM
(nitisinone) tablets

2 mg

Rx only 60 tablets

Principal Display Panel – 2 mg Bottle Label

NDC 70709-112-60

HARLIKUTM
(nitisinone) tablets

2 mg

Rx only CYCLE PHARMA 60 tablets